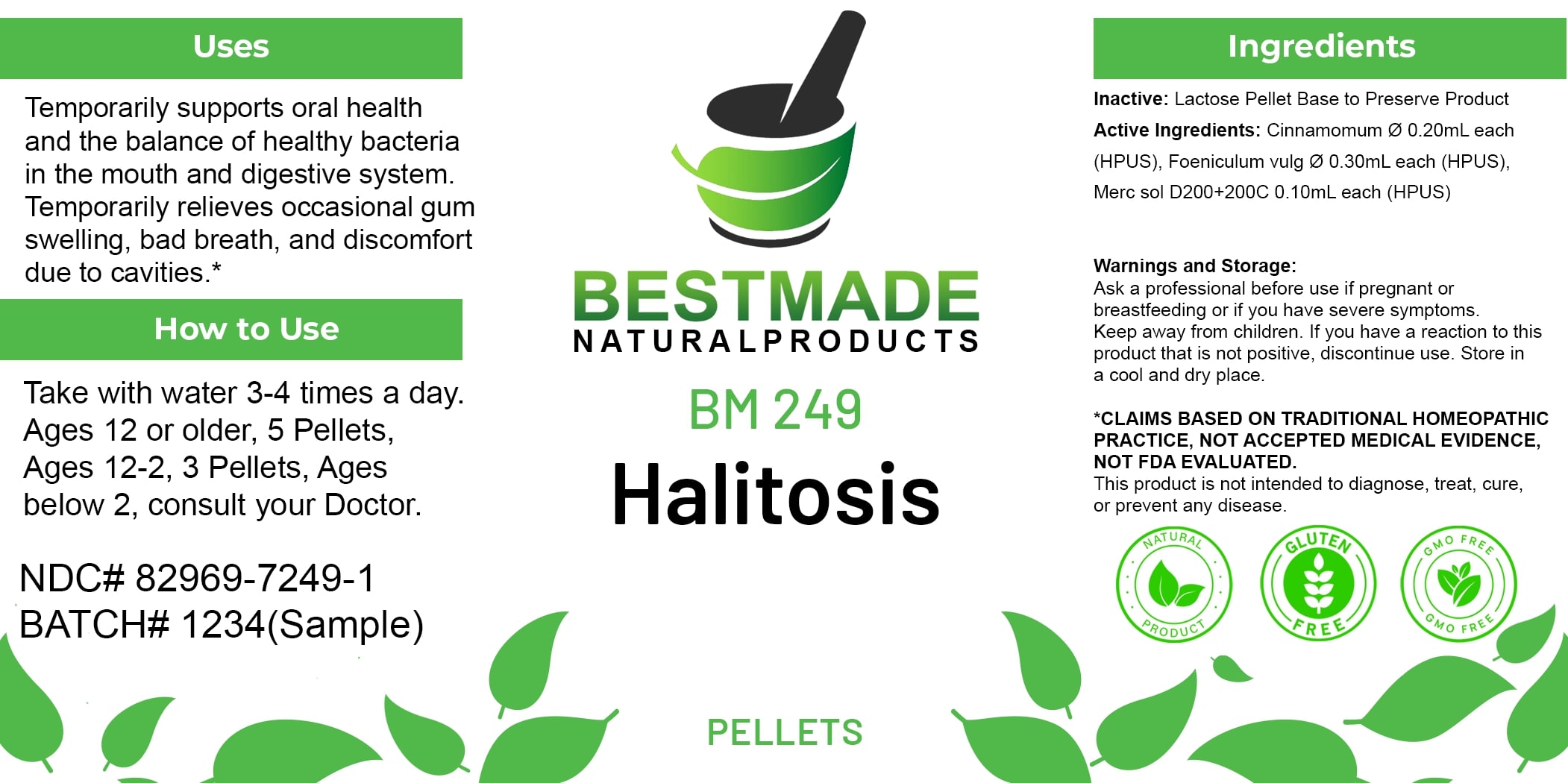 DRUG LABEL: Bestmade Natural Products BM249 Pellets
NDC: 82969-7249 | Form: TABLET, SOLUBLE
Manufacturer: Bestmade Natural Products
Category: homeopathic | Type: HUMAN OTC DRUG LABEL
Date: 20250408

ACTIVE INGREDIENTS: CINNAMON 30 [hp_C]/30 [hp_C]; FOENICULUM VULGARE FRUIT 30 [hp_C]/30 [hp_C]; MERCURIUS SOLUBILIS 30 [hp_C]/30 [hp_C]
INACTIVE INGREDIENTS: SUCROSE 30 [hp_C]/30 [hp_C]

BM249 Pellets

DOSAGE AND ADMINISTRATION

How to Use

Take with water 3-4 times a day. Ages 12 or older, 5 Pellets, Ages 12-2, 3 Pellets, Ages below 2, consult your Doctor.

INACTIVE INGREDIENT

Ingredients

Inactive: Lactose Pellet Base to Preserve Product

ACTIVE INGREDIENT

Active Ingredients: Cinnamomum ø 0.20ml each (HPUS), Foeniculum vulg ø 0.30ml each (HPUS), Merc sol D200+200C 0.10ml each (HPUS)

Uses

Temporarily supports oral health and the balance of healthy bacteria in the mouth and digestive system. Temporarily relieves occasional gum swelling, bad breath, and discomfort due to cavities.*

*CLAIMS BASED ON TRADITIONAL HOMEOPATHIC PRACTICE. NOT ACCEPTED MEDICAL EVIDENCE. NOT FDA EVALUATED.

This product is not intended to diagnose, treat, cure, or prevent any disease.

Uses

Temporarily supports oral health and the balance of healthy bacteria in the mouth and digestive system. Temporarily relieves occasional gum swelling, bad breath, and discomfort due to cavities.*

*CLAIMS BASED ON TRADITIONAL HOMEOPATHIC PRACTICE. NOT ACCEPTED MEDICAL EVIDENCE. NOT FDA EVALUATED.

This product is not intended to diagnose, treat, cure, or prevent any disease.

KEEP OUT OF REACH OF CHILDREN

Warnings and Storage:

Ask a professional before use if pregnant or breastfeeding or if you have severe symptoms. Keep away from children. If you have a reaction to this product that is not positive, discontinue use. Store in a cool and dry place.

Warnings and Storage:

Ask a professional before use if pregnant or breastfeeding or if you have severe symptoms. Keep away from children. If you have a reaction to this product that is not positive, discontinue use. Store in a cool and dry place.

*CLAIMS BASED ON TRADITIONAL HOMEOPATHIC PRACTICE. NOT ACCEPTED MEDICAL EVIDENCE. NOT FDA EVALUATED.

This product is not intended to diagnose, treat, cure, or prevent any disease.

Entire package label